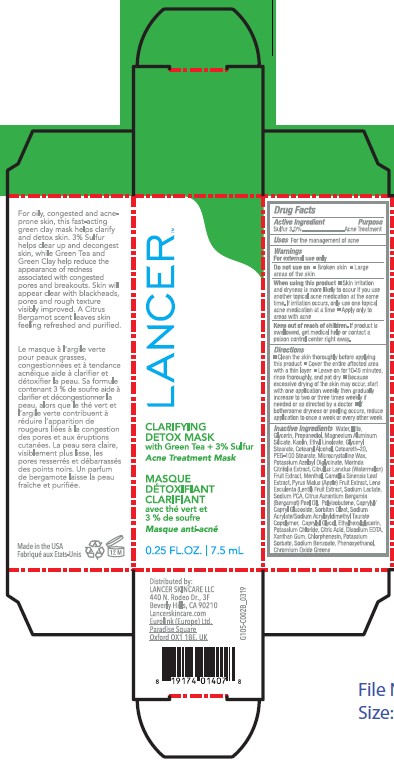 DRUG LABEL: Sulfur
NDC: 67923-106 | Form: CREAM
Manufacturer: Vege Labs LLC
Category: otc | Type: HUMAN OTC DRUG LABEL
Date: 20250313

ACTIVE INGREDIENTS: SULFUR 3 mg/100 mg
INACTIVE INGREDIENTS: CITRIC ACID; CETEARYL ALCOHOL; SODIUM BENZOATE; PHENOXYETHANOL; ILLITE; POTASSIUM AZELOYL DIGLYCINATE; XANTHAN GUM; MORINDA CITRIFOLIA FRUIT; CITRULLUS LANATUS WHOLE; MENTHOL; SODIUM PCA; CITRUS AURANTIUM BERGAMIA (BERGAMOT) PEEL OIL; LENTIL; CAPRYLYL/CAPRYL GLUCOSIDE; SORBITAN OLEATE; CAPRYLYL GLYCOL; POTASSIUM CHLORIDE; WATER; GLYCERIN; KAOLIN; PYRUS MALUS (APPLE) FRUIT; SODIUM LACTATE; ETHYL LINOLEATE; SODIUM ACRYLATE/SODIUM ACRYLOYLDIMETHYLTAURATE COPOLYMER (4000000 MW); MICROCRYSTALLINE WAX; CAMELLIA SINENSIS LEAF; HYDROGENATED POLYISOBUTENE (450 MW); PROPANEDIOL; ETHYLHEXYLGLYCERIN; MAGNESIUM ALUMINUM SILICATE; CETEARETH-20; CHROMIUM OXIDE GREENS; POTASSIUM SORBATE; GLYCERYL STEARATE; PEG-100 STEARATE; CALCIUM DISODIUM EDTA; CHLORPHENESIN

Active Ingredient

Sulfur 3.0%

Purpose

Acne Treatment

Uses

For the management of acne

Warnings

For external use only

Do not use on

Broken skin, Large areas of the skin

When using this product

Skin irritation and dryness is more likely to occur if you use another topical acne medication at the same time. If irritation occurs, only use one topical acne medication at a time. Apply only to areas with acne

Keep out of reach of children

If product is swallowed, get medical help or contact a poison control center right away

Directions

Clean the skin thoroughly before applying this product. Cover the entire affected area with a thin layer. Leave on for 10-15 minutes, rinse thoroughly, and pat dry. Because excessive drying of the skin may occur, start with one application weekly then gradually increase to two or three times weekly if needed or as directed by a doctor. If bothersome dryness or peeing occurs, reduce application to once a week or every other week.

Inactive Ingredients

Water, Illite, Glycerin, Propanediol, Magnesium Aluminum Silicate, Caolin, Ethyl Linoleate, Glyceryl Stearate, Cetearyl Alcohol, Ceteareth-20, PEG-100 Stearate, Microcrystalline Wax, Potassium Azeloyl Diglycinate, Morinda Citrifolia Extract, Citrullus Lanatus (Watermelon) Fruit Extract, Menthol, Camellia Sinensis Leaf Extract, Pyrus Malus (Apple) Fruit Extract, Lens Esculenta (Lentil) Fruit Extract, Sodium Lactate, Sodium PCA, Citrus Aurantium Bernamia (Bergamot) Peel Oil, Polyisobutene, Caprylyl/Capryl Glucoside, Sorbitan Oleat, Sodium Acrylate/Sodium Acryloyldimethyl Taurate Copolymer, Caprylyl Glycol, Ethylhexylglycerin, Potassium Chloride, Citric Acid, Disodium EDTA, Xanthan Gum, Chlorphenesin, Potassium Sorbate, Sodium Benzoate, Phenoxyethanol, Chromium Oxide Greens